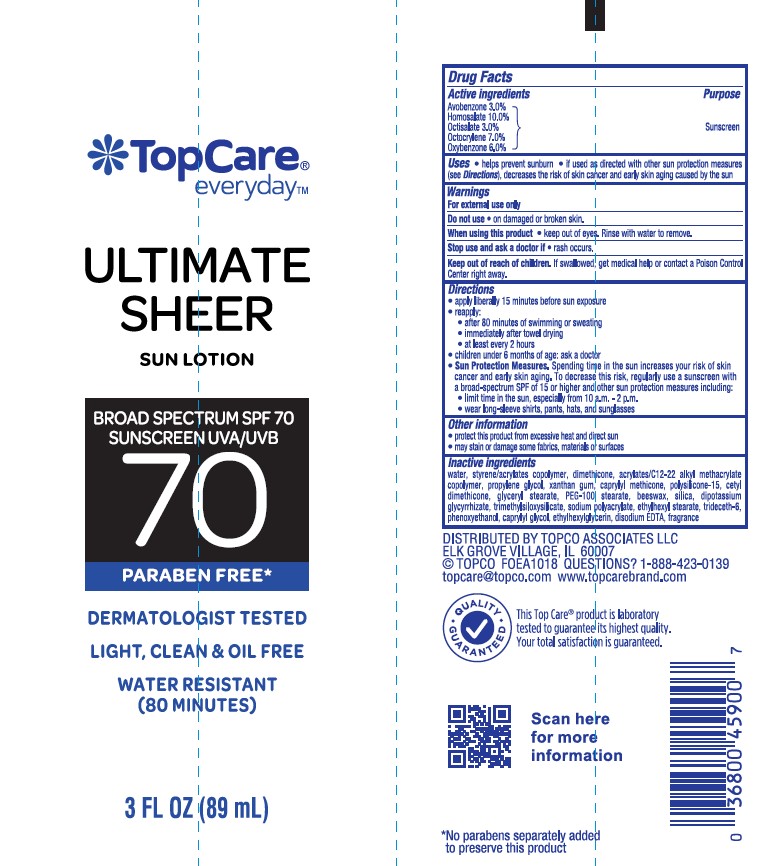 DRUG LABEL: TopCare Everyday Ultimate Sheer Sun Broad Spectrum SPF 70
NDC: 36800-093 | Form: LOTION
Manufacturer: TOPCO ASSOCIATES LLC
Category: otc | Type: HUMAN OTC DRUG LABEL
Date: 20241015

ACTIVE INGREDIENTS: HOMOSALATE 100 mg/1 mL; OCTOCRYLENE 70 mg/1 mL; OCTISALATE 30 mg/1 mL; AVOBENZONE 30 mg/1 mL; OXYBENZONE 60 mg/1 mL
INACTIVE INGREDIENTS: BUTYL ACRYLATE/C16-C20 ALKYL METHACRYLATE/METHACRYLIC ACID/METHYL METHACRYLATE COPOLYMER; EDETATE DISODIUM; TRIDECETH-6; TRIMETHYLSILOXYSILICATE (M/Q 0.8-1.0); XANTHAN GUM; ETHYLHEXYL STEARATE; CAPRYLYL TRISILOXANE; DIMETHICONE; WATER; BUTYL METHACRYLATE/METHYL METHACRYLATE/METHACRYLIC ACID/STYRENE CROSSPOLYMER; SILICON DIOXIDE; POLYSILICONE-15; GLYCERYL STEARATE/PEG-100 STEARATE; SODIUM POLYACRYLATE (8000 MW); PROPYLENE GLYCOL; GLYCYRRHIZINATE DIPOTASSIUM; WHITE WAX; ETHYLHEXYLGLYCERIN; PHENOXYETHANOL; CETYL DIMETHICONE 45; CAPRYLYL GLYCOL

TopCare Everyday Ultimate Sheer Sun Lotion Broad Spectrum SPF 70

Active ingredients

Avobenzone 3.0%

Homosalate 10.0%

Octisalate 3.0%

Octocrylene 7.0%

Oxybenzone 6.0%

Purpose

Sunscreen

Uses

- helps prevent sunburn
- if used as directed with other sun protection measures (see Directions), decreases the risk of skin cancer and early skin aging caused by the sun

Warnings

For external use only

Do not use

- on damaged or broken skin.

When using this product

- keep out of eyes. Rinse with water to remove.

Stop use and ask a doctor

- if rash occurs.

Keep out of reach of children.

If swallowed, get medical help or contact a Poison Control Center right away.

Directions

- apply liberally 15 minutes before sun exposure

reapply:
• after 80 minutes of swimming or sweating
• immediately after towel drying
• at least every 2 hours

- children under 6 months of age: Ask a doctor

Sun Protection Measures. Spending time in the sun increases your risk of skin cancer and early skin aging. To decrease this risk, regularly use a sunscreen with a Broad Spectrum SPF value of 15 or higher and other sun protection measures including:
• limit time in the sun, especially from 10 a.m. - 2 p.m.
• wear long-sleeved shirts, pants, hats, and sunglasses

Other information

• protect the product in this container from excessive heat and direct sun
• may stain or damage some fabrics, materials or surfaces

Inactive ingredients

water, styrene/acrylates copolymer, dimethicone, acylates/C12-22 alkyl methacrylate copolymer, propylene glycol, xanthan gum, capryl methicone, polysilicone-15, cetyl dimethicone, glyceryl stearate, PEG-100 stearate, beeswax, silica, dipotassium glycyrrhizate, trimethylsiloxysilicate, sodium polyacrylate, ethylhexyl stearate, trideceth-6, phenoxyethanol, caprylyl glycol, ethylhexylglycerin, disodium EDTA, fragrance

PACKAGE LABEL

TopCare Everyday Ultimate Sheer Sun Lotion Broad Spectrum SPF 70

3.0 FL OZ (89 mL)

-09